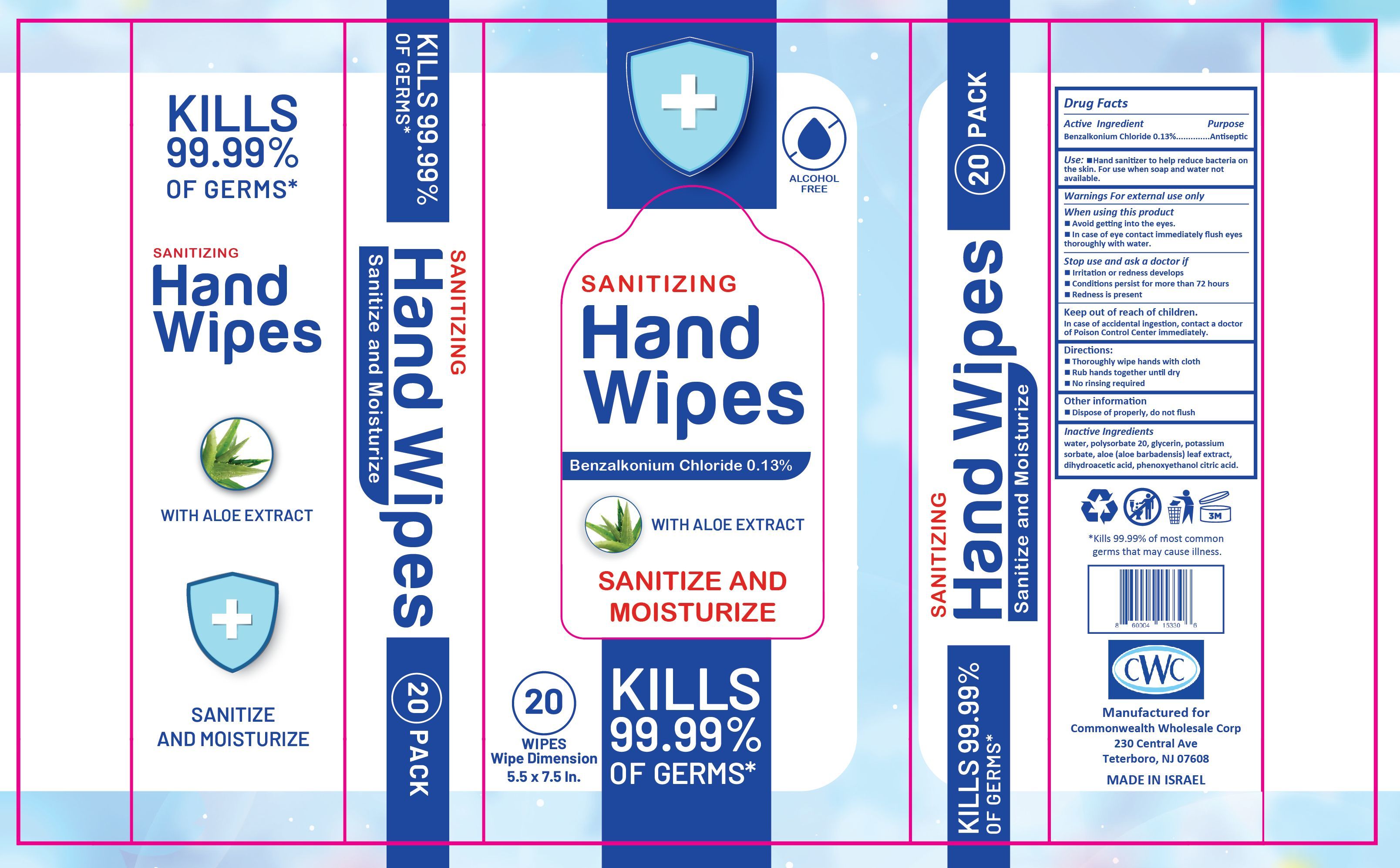 DRUG LABEL: Sanitizing Hand Wipes
NDC: 77645-001 | Form: CLOTH
Manufacturer: DYNAMIC WIPE INDUSTRIES LTD.
Category: otc | Type: HUMAN OTC DRUG LABEL
Date: 20200701

ACTIVE INGREDIENTS: BENZALKONIUM CHLORIDE 0.13 g/1 1
INACTIVE INGREDIENTS: POLYSORBATE 20; GLYCERIN; POTASSIUM SORBATE; DEHYDROACETIC ACID; PHENOXYETHANOL; CITRIC ACID MONOHYDRATE; ALOE VERA LEAF; WATER

Dynamic CWC Hand Wipes

Active ingredient

Benzalkonium chloride 0.13%

Purpose

Antiseptic

Use

■ Hand sanitizer to help reduce bacteria on the skin. For use when soap and water not available

Warnings

For external use only

When using this product

■ Avoid getting into the eyes.

■ In case of eye contact immediately flush eyes thoroughly with water.

Stop use and ask a doctor if

■ Irritation or redness develops

■ Conditions persist for more than 72 hours

■ Redness is present

Keep out of reach of children

In case of accidental ingestion contact a doctor or Poison Control Center immediately.

Directions

■ Thoroughly wipe hands with cloth

■ Rub hands together until dry

■ No rinsing required

Other information

■ Dispose of properly, do not flush

Inactive ingredients

water, polysorbate 20, glycerin, potassium sorbate, aloe (aloe barbadensis) leaf extract, dihydroacetic acid, phenoxyethanol, citric acid